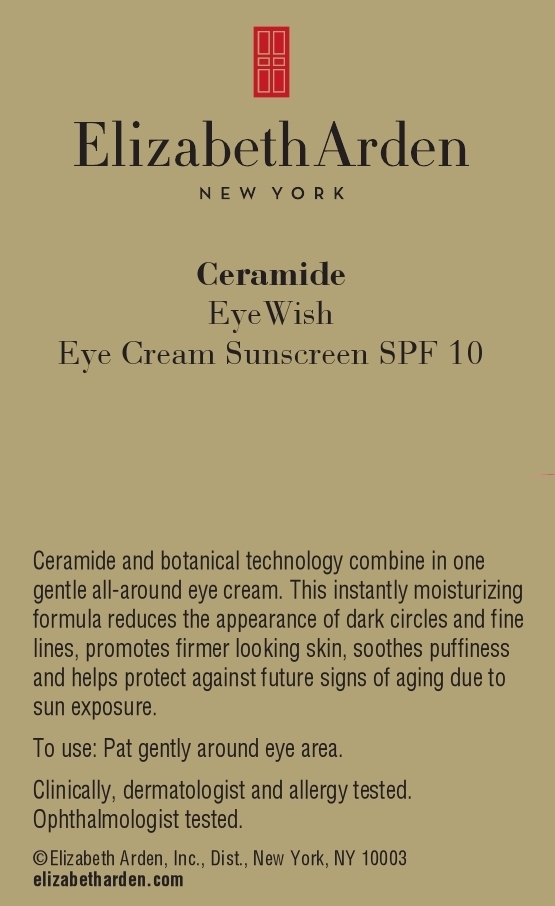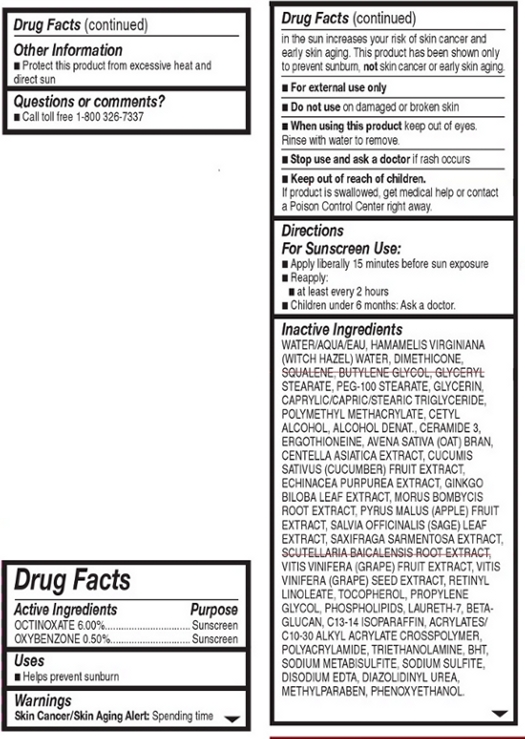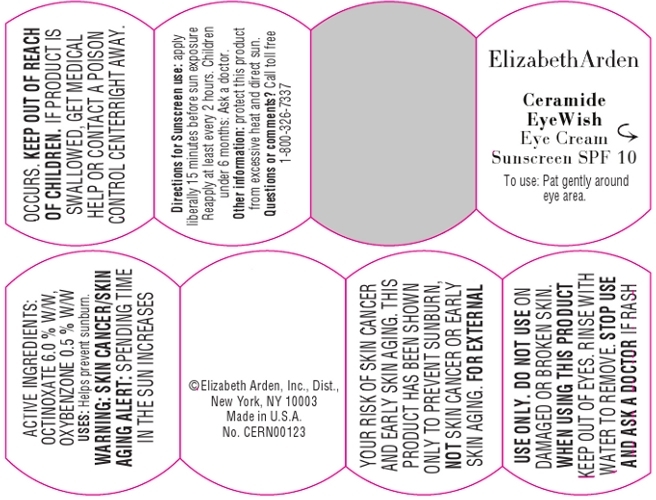 DRUG LABEL: Ceramide EyeWish Eye Sunscreen SPF 10
NDC: 67938-0772 | Form: CREAM
Manufacturer: Elizabeth Arden, Inc
Category: otc | Type: HUMAN OTC DRUG LABEL
Date: 20121022

ACTIVE INGREDIENTS: OCTINOXATE 0.852 g/14.2 g; OXYBENZONE 0.071 g/14.2 g
INACTIVE INGREDIENTS: WATER; HAMAMELIS VIRGINIANA LEAF WATER; DIMETHICONE; SQUALENE; BUTYLENE GLYCOL; GLYCERYL MONOSTEARATE; PEG-100 STEARATE; GLYCERIN; CETYL ALCOHOL; ALCOHOL; TROLAMINE; OXYBENZONE; TOCOPHEROL; CARBOMER INTERPOLYMER TYPE A (55000 MPA.S); POLYACRYLAMIDE (10000 MW); SAXIFRAGA STOLONIFERA LEAF; WINE GRAPE; C13-14 ISOPARAFFIN; DIAZOLIDINYL UREA; PROPYLENE GLYCOL; CUCUMBER; RETINYL LINOLEATE; EDETATE DISODIUM; OMEGA-3 FATTY ACIDS; LAURETH-7; CERAMIDE 3; SODIUM METABISULFITE; SODIUM SULFITE; SALVIA OFFICINALIS FLOWERING TOP; GINKGO; APPLE; MORUS AUSTRALIS ROOT; SCUTELLARIA BAICALENSIS ROOT; METHYLPARABEN; CENTELLA ASIATICA; PHENOXYETHANOL; OAT BRAN; BUTYLATED HYDROXYTOLUENE; ECHINACEA PURPUREA; VITIS VINIFERA SEED; ERGOTHIONEINE

BC0772

DESCRIPTION

Ceramide and botanical technology combine in one gentle all-around eye cream. This instantly moisturizing formula reduces the appearance of dark circles and fine lines, promotes firmer looking skin, soothes puffiness, and helps protect against future signs of aging due to sun exposure.

INDICATIONS AND USAGE

To Use: Pat gently all around eye area.

For Sunscreen Use: Apply liberally 15 minutes before sun exposure. Reapply at least every 2 hours.

Childre Under 6: Ask a doctor.

WARNINGS

Skin Cancer/Skin Aging Alert: Spending time in the sun increases your risk of skin cancer and early skin aging. This product has been show to prevent sunburn, not skin cancer or early skin aging.

For external use only.

Do not use on damaged or broken skin.

When using this product, keep out of eyes. Rinse with water to remove.

Stop use and ask a doctor if rash occurs.

OTC - ACTIVE INGREDIENT

Active Ingredients: Octinoxate 6.00% , Oxybenzone 0.50%.

INACTIVE INGREDIENT

Other Ingredients: Water, Hamamelis Virginiana (Witch Hazel) Water, Dimethicone, Squalene, Butylene Glycol, Glyceryl Stearate, PEG-100 Stearate, Glycerin, Caprylic/Capric/Stearic Triglyceride, Polymethyl Methacrylate, Cetyl Alcohol, Alcohol Denat., Ceramide 3, Ergothioneine, Avena Sativa (Oat) Bran, Centella Asiatica Extract, Cucumin Sativus (Cucumber) Fruit Extract, Echinacea Purpurea Extract, Ginkgo Biloba Leaf Extract, Morus Bombycis Root Extract, Pyrus Malus (Apple) Fruit Extract, Salvia Officinalis (Sage) Leaf Extract, Scutellaria Baicalensis Root Extract, Vitis Vinifera (Grape) Fruit Extratct, Vitin Vinifera (Grape) Seed Extract, Retinyl Linoleate, Tocopherol, Propylene Glycol, Phospholipids, Laureth-7, Beta-Glucan, C13-14 Isoparaffin, Acrylates/C10-30 Alkyl Acrylate Crosspolymer, Polyacrylamide, Triethanolamine, BHT, Sodium Metabisulfite, Sodium Sulfite, Disodium EDTA, Diazolidnyl Urea, Methyl Paraben, Phenoxyethanol.

DOSAGE & ADMINISTRATION

Pat around eye area.

OTC - KEEP OUT OF REACH OF CHILDREN

Keep out of reach of children. If product is swallowed, get medical help or contact a Poison Control Center right away.

OTC - PURPOSE

Provides SPF 10 sun protection.

OTC - WHEN USING

Keep out of eyes.